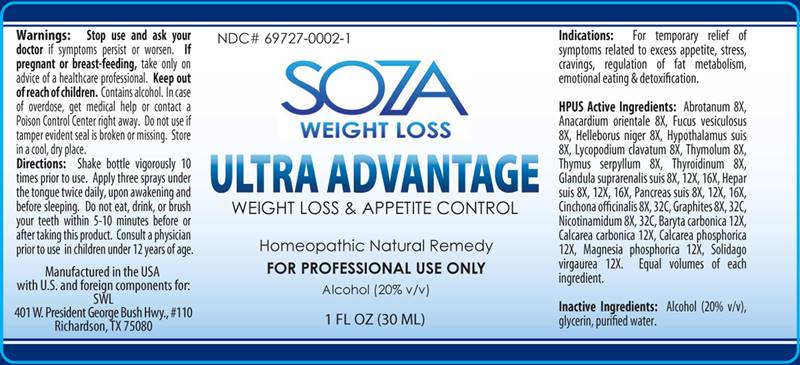 DRUG LABEL: Ultra Advantage
NDC: 69727-0002 | Form: LIQUID
Manufacturer: ELTTAC Inc DBA SWL
Category: homeopathic | Type: HUMAN OTC DRUG LABEL
Date: 20181212

ACTIVE INGREDIENTS: ARTEMISIA ABROTANUM FLOWERING TOP 8 [hp_X]/1 mL; SEMECARPUS ANACARDIUM JUICE 8 [hp_X]/1 mL; FUCUS VESICULOSUS 8 [hp_X]/1 mL; HELLEBORUS NIGER ROOT 8 [hp_X]/1 mL; SUS SCROFA HYPOTHALAMUS 8 [hp_X]/1 mL; LYCOPODIUM CLAVATUM SPORE 8 [hp_X]/1 mL; THYMOL 8 [hp_X]/1 mL; THYMUS SERPYLLUM 8 [hp_X]/1 mL; THYROID, BOVINE 8 [hp_X]/1 mL; SUS SCROFA ADRENAL GLAND 8 [hp_X]/1 mL; PORK LIVER 8 [hp_X]/1 mL; SUS SCROFA PANCREAS 8 [hp_X]/1 mL; CINCHONA OFFICINALIS BARK 8 [hp_X]/1 mL; GRAPHITE 8 [hp_X]/1 mL; NIACINAMIDE 8 [hp_X]/1 mL; BARIUM CARBONATE 12 [hp_X]/1 mL; OYSTER SHELL CALCIUM CARBONATE, CRUDE 12 [hp_X]/1 mL; TRIBASIC CALCIUM PHOSPHATE 12 [hp_X]/1 mL; MAGNESIUM PHOSPHATE, DIBASIC TRIHYDRATE 12 [hp_X]/1 mL; SOLIDAGO VIRGAUREA FLOWERING TOP 12 [hp_X]/1 mL
INACTIVE INGREDIENTS: WATER; ALCOHOL; GLYCERIN

Drug Facts:

ACTIVE INGREDIENTS:

Abrotanum (Artemisia Abrotanum) 8X, Anacardium Orientale 8X, Fucus Vesiculosus 8X, Helleborus Niger 8X, Hypothalamus Suis 8X, Lycopodium Clavatum 8X, Thymolum 8X, Thymus Serpyllum 8X, Thyroidinum (Bovine) 8X, Glandula Suprarenalis Suis 8X, 12X, 16X, Hepar Suis 8X, 12X, 16X, Pancreas Suis 8X, 12X, 16X, Cinchona Officinalis 8X, 32C, Graphites 8X, 32C, Nicotinamidum 8X, 32C, Baryta Carbonica 12X Calcarea Carbonica 12X, Calcarea Phosphorica 12X, Magnesia Phosphorica 12X, Solidago Virgaurea 12X.

INDICATIONS:

For temporary relief of symptoms related to excess appetite, stress, cravings, regulation of fat metabolism, emotional eating & detoxification.

WARNINGS:

Stop use and ask your doctor if symptoms persist or worsen.

In case of overdose, get medical help or contact a Poison Control Center right away.

If pregnant or breast-feeding, take only on advice of a physician

Keep out of reach of children.

OTHER INFORMATION:

Store in a cool, dry place, Tamper resistant for your protection. Use only if safety seal is intact.

Keep out of reach of children. In case of overdose, get medical help or contact a Poison Control Center right away.

DIRECTIONS:

1-10 drops under the tongue, 3 times a day or as directed by a health professional. Consult a physician for use in children under 12 years of age.

INDICATIONS:

For temporary relief of symptoms related to excess appetite, stress, cravings, regulation of fat metabolism, emotional eating & detoxification.

INACTIVE INGREDIENTS:

Alcohol (20% v/v), glycerin, purified water.

QUESTIONS:

Manufactured in the USA

with U.S. and foreign components for:

SWL

401 W. President George Bush Hwy., #110

Richardson, TX, 75080

PACKAGE LABEL DISPLAY:

NDC 69719-0002-1

SOZA

WEIGHT LOSS

ULTRA ADVANTAGE

WEIGHTLOSS & APPETITE CONTROL

Homeopathic Natural Remedy

FOR PROFESSIONAL USE ONLY

1 FL OZ (30 ML)